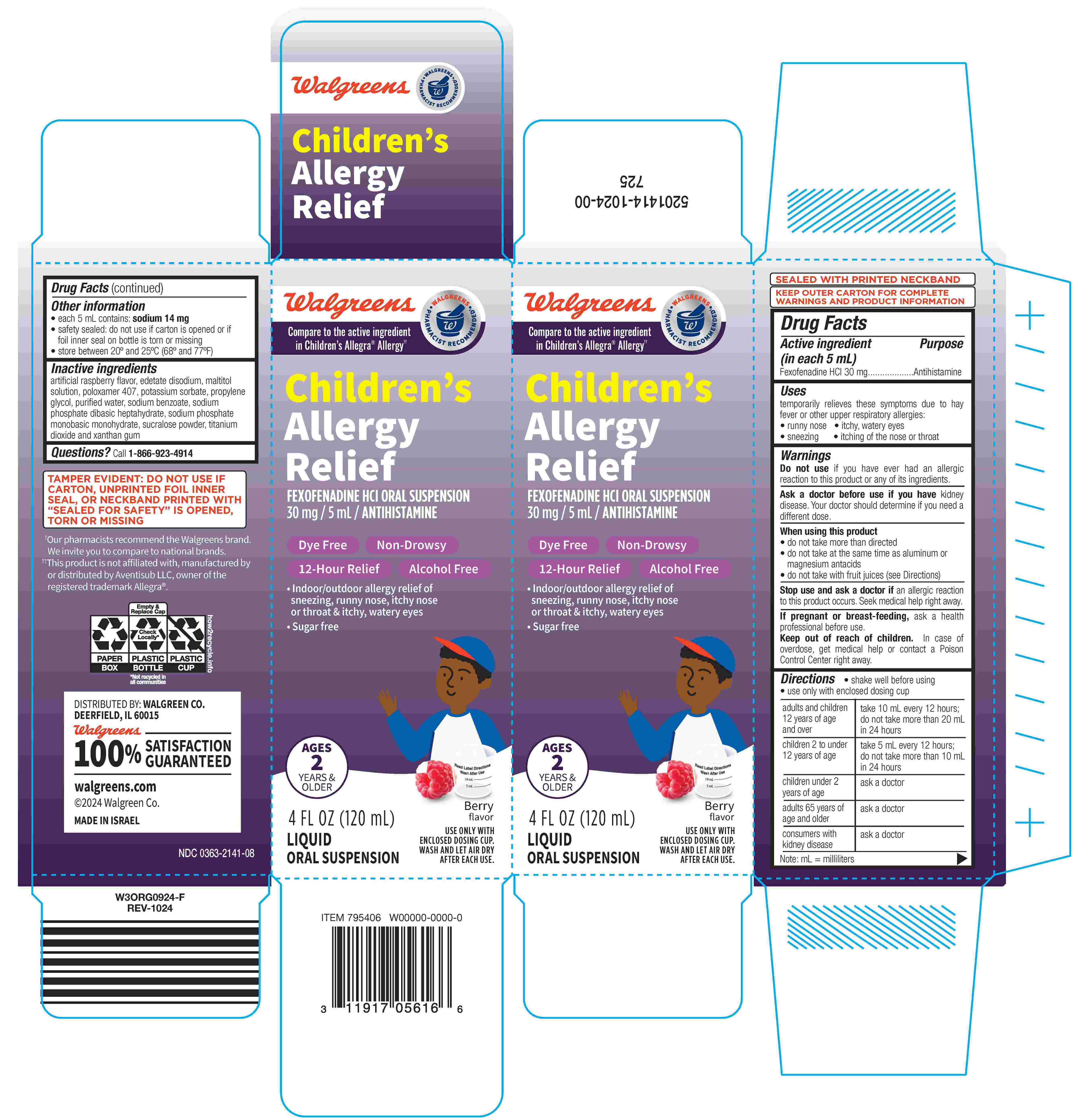 DRUG LABEL: Childrens Fexofenadine Hydrochloride
NDC: 0363-2141 | Form: SUSPENSION
Manufacturer: Walgreens Company
Category: otc | Type: HUMAN OTC DRUG LABEL
Date: 20250611

ACTIVE INGREDIENTS: FEXOFENADINE HYDROCHLORIDE 30 mg/5 mL
INACTIVE INGREDIENTS: EDETATE DISODIUM; MALTITOL; POLOXAMER 407; PROPYLENE GLYCOL; WATER; SODIUM PHOSPHATE, DIBASIC, HEPTAHYDRATE; SODIUM PHOSPHATE, MONOBASIC, MONOHYDRATE; SUCRALOSE; POTASSIUM SORBATE; TITANIUM DIOXIDE; XANTHAN GUM; SODIUM BENZOATE

Children's Fexofenadine HCl
Allergy

Drug Facts

Active ingredient (in each 5 mL)

Fexofenadine HCl 30 mg

Purpose

Antihistamine

Uses

temporarily relieves these symptoms due to hay fever or other upper respiratory allergies:

- runny nose
- itchy, watery eyes
- sneezing
- itching of the nose or throat

Warnings

Do not use if you have ever had an allergic reaction to this product or any of its ingredients.

Ask a doctor before use if you have kidney disease. Your doctor should determine if you need a different dose.

When using this product

- do not take more than directed
- do not take at the same time as aluminum or magnesium antacids
- do not take with fruit juices (see Directions)

Stop use and ask a doctor if an allergic reaction to this product occurs. Seek medical help right away.

PREGNANCY OR BREAST FEEDING

If pregnant or breast-feeding, ask a health professional before use.

Keep out of reach of children. In case of overdose, get medical help or contact a Poison Control Center right away.

Directions

- shake well before using
- use only with enclosed dosing cup

adults and children 12 years of age and over | take 10 mL every 12 hours; do not take more than 20 mL in 24 hours
children 2 to under 12 years of age | take 5 mL every 12 hours; do not take more than 10 mL in 24 hours
children under 2 years of age | ask a doctor
adults 65 years of age and older | ask a doctor
consumers with kidney disease | ask a doctor
Note: mL = milliliters

Other information

- each 5 mL contains: sodium 14 mg
- safety sealed: do not use if carton is opened or if foil inner seal on bottle is torn or missing
- store between 20º and 25ºC (68º and 77ºF)

Inactive ingredients

artificial raspberry flavor, edetate disodium, maltitol solution, poloxamer 407, potassium sorbate, propylene glycol, purified water, sodium benzoate, sodium phosphate dibasic heptahydrate, sodium phosphate monobasic monohydrate, sucralose powder, titanium dioxide and xanthan gum

Questions?

Call 1-866-923-4914

DISTRIBUTED BY: WALGREEN CO.
DEERFIELD, IL 60015

PRINCIPAL DISPLAY PANEL - 120 mL Bottle Carton

NDC 0363-2141-08

Children's
Allergy Relief
Fexofenadine HCl
Oral Suspension,
30 mg/ 5 mL

4 FL OZ

(120 mL)